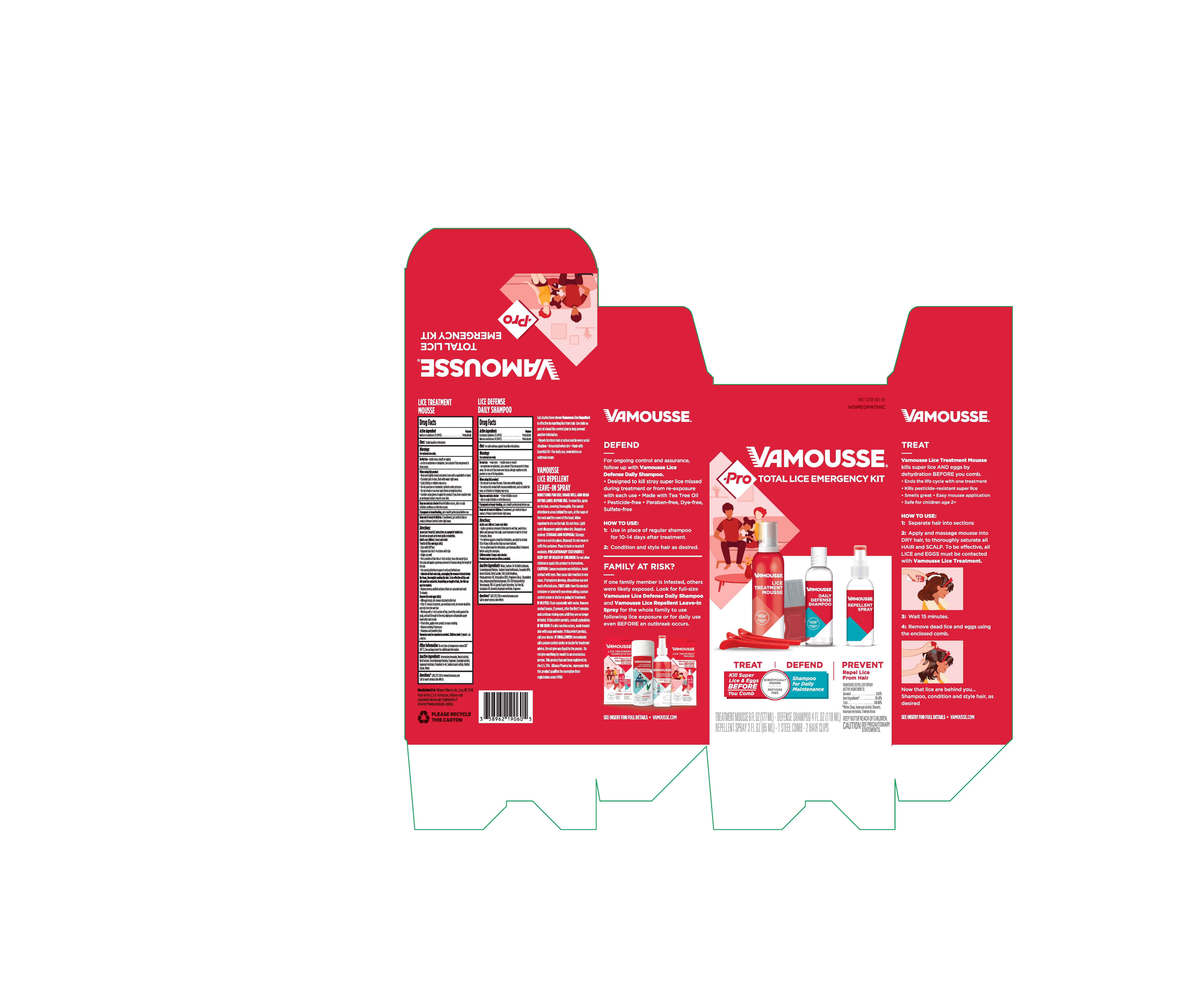 DRUG LABEL: Vamousse Pro Total Lice Emergency Kit
NDC: 72238-005 | Form: KIT | Route: TOPICAL
Manufacturer: Alliance Pharma Inc.
Category: homeopathic | Type: HUMAN OTC DRUG LABEL
Date: 20241011

ACTIVE INGREDIENTS: SODIUM CHLORIDE 2 [hp_X]/1 mL; EUCALYPTUS GLOBULUS LEAF 2 [hp_X]/1 mL; SODIUM CHLORIDE 2 [hp_X]/1 mL
INACTIVE INGREDIENTS: BENZYL ALCOHOL; SODIUM LAURYL SULFATE; TRIETHYL CITRATE; BUTYL LACTATE; GERANIOL; COCAMIDOPROPYL BETAINE; LIQUEFIED PETROLEUM GAS; AMMONIUM BENZOATE; VANILLIN; WATER; ISOPROPYL MYRISTATE; ISOPROPYL ALCOHOL; COCO DIISOPROPANOLAMIDE; SODIUM COCOYL ISETHIONATE; CAPRYLOCAPROYL POLYOXYLGLYCERIDES 6; DIAZOLIDINYL UREA; GERANIOL; ANHYDROUS CITRIC ACID; WATER; IODOPROPYNYL BUTYLCARBAMATE; SODIUM C14-16 OLEFIN SULFONATE; PEG-150 PENTAERYTHRITYL TETRASTEARATE; EUCALYPTUS OIL; POLYQUATERNIUM-10 (125 MPA.S AT 2%); EDETATE SODIUM; ISOPROPYL MYRISTATE; PROPYLENE GLYCOL; TEA TREE OIL; BENZYL ALCOHOL; BUTYL LACTATE; COCAMIDOPROPYL BETAINE

19060CTNA Pro Total Lice Emergency Kit (Mousse)

ACTIVE INGREDIENT

Vamousse Lice Treatment:

Natrum Muriaticum 2X (HPUS)

Vamousse Lice Defense Daily Shampoo:

Eucalyptus globulus 2X (HPUS)

Natrum Muriaticum 2X (HPUS)

Purpose

Pediculicide

INDICATIONS AND USAGE

Vamousse Lice Treatment:

Treats head lice infestation

Vamousse Lice Defense Daily Shampoo:

For daily defense against head lice infestations

WARNINGS

For external use only

DO NOT USE

Vamouss Lice Treatment:

Do Not Use near eyes, inside nose, mouth, or vagina, on lice in eyebrows or eyelashes. See a doctor if lice are present in these areas.

Vamousse Lice Defense Daily Shampoo:

Do not use near eyes, inside nose or mouth, on eyebrows or eyelashes. See a doctor if lice are present in these areas. Do not use if you have ever had an allergic reaction to this product or any of its ingredients.

WHEN USING

Vamousse Lice Treatment
When using this product Keep eyes tightly closed and protect eyes with a washcloth or towel.
If product gets in eyes, flush with water right away.
Scalp itching or redness may occur.
Do not puncture or incinerate, contents under pressure.
Do not smoke or use near open flame or heated surface.
Consider using gloves to apply the product if you have sensitive skin as prolonged contact may dry your skin.

Vamousse Lice Defense Daily Shampoo:

When using this product Do not use near the eyes. Close eyes while applying.

Do not permit contact with mucous membranes, such as inside the nose, as irritation or stinging may occur.

Stop use and ask a doctor if eye irritation occurs, skin or scalp irritation continues or infection occurs.

PREGNANCY OR BREAST FEEDING

If pregnant or breastfeeding, ask a health professional before use.

Keep out of reach of children. If swallowed, get medical help or contact a Poison Control Center right away.

DOSAGE AND ADMINISTRATION

Vamousse Lice Treatment:

Directions

Important: Read ALL instructions on pamphlet inside box.

Do not use on pets or to treat pubic or body lice.

Adults and children 2 years and older:

Treat to kill lice and eggs (nits):

- Start with DRY hair
- Separate hair into 3-4 sections with clips.
- Shake can well.
- Part a section of hair into a 1-inch section, focus the nozzle tip on the scalp and apply a generous amount of mousse along the length of the hair
- Pay special attention to nape of the neck and behind the ears
- Saturate all hair and scalp, massaging the mousse to break down the foam, thoroughly soaking the hair. To be effective all lice and nits must be contacted. Depending on the length of hair, the full can may be needed.
- Repeat process until all sections of hair are saturated and wait 15 minutes.

Remove lice and eggs (nits):

- Although dead, nits remain attached to the hair.
- After 15-minute treatment, use enclosed comb, to remove dead lice and nits from the wet hair.
- Working with a 1-inch section of hair, insert the comb against the scalp, and pull through to the end, wiping on a disposable paper towel after each stroke.
- If hair dries, apply more product to ease combing.
- Repeat combing if necessary
- Shampoo and towel dry hair.

Vamousse may be repeated as needed. Children under 2 years: ask a doctor.

Vamousse Lice Defense Daily Shampoo:

Adults and children 2 years and older:

- Apply a generous amount of shampoo to wet hair, work into a lather and massage into scalp. Leave shampoo in hair for at least 3 minutes. Rinse.
- For defense against head lice infestation, use daily for at least 10 to 14 days to kill any lice that may have hatched.
- For an active head lice infestation, use Vamousse Lice Treatment before using this shampoo

Children under 2 years: ask a doctor/

Product may be used as often as needed.

INACTIVE INGREDIENT

Vamousse Lice Treatment

Inactive Ingredients

Ammonium benzoate, Benzyl alcohol, Butyl lactate, Cocomidopropyl betaine, Fragrance, Isopropyl alcohol, Isopropyl myristate, Propellant A-46, Sodium lauryl sulfate, Triethyl citrate, Water

Vamousse Lice Defense Daily Shampoo:

Inactive Ingredients

Benzyl alcohol, Butyl lactate, Cocomidopropyl betaine, Diazolidinyl urea, Fragrance, Isopropyl myristate, Sodium Chloride, Sodium lauryl sulfate, Water

QUESTIONS

Questions? 1.855.373.7210 or www.VamousseLice.com. Call to report serious side effects.